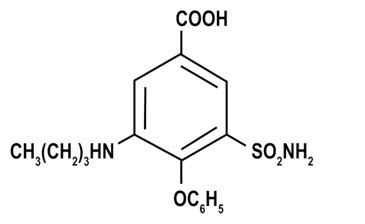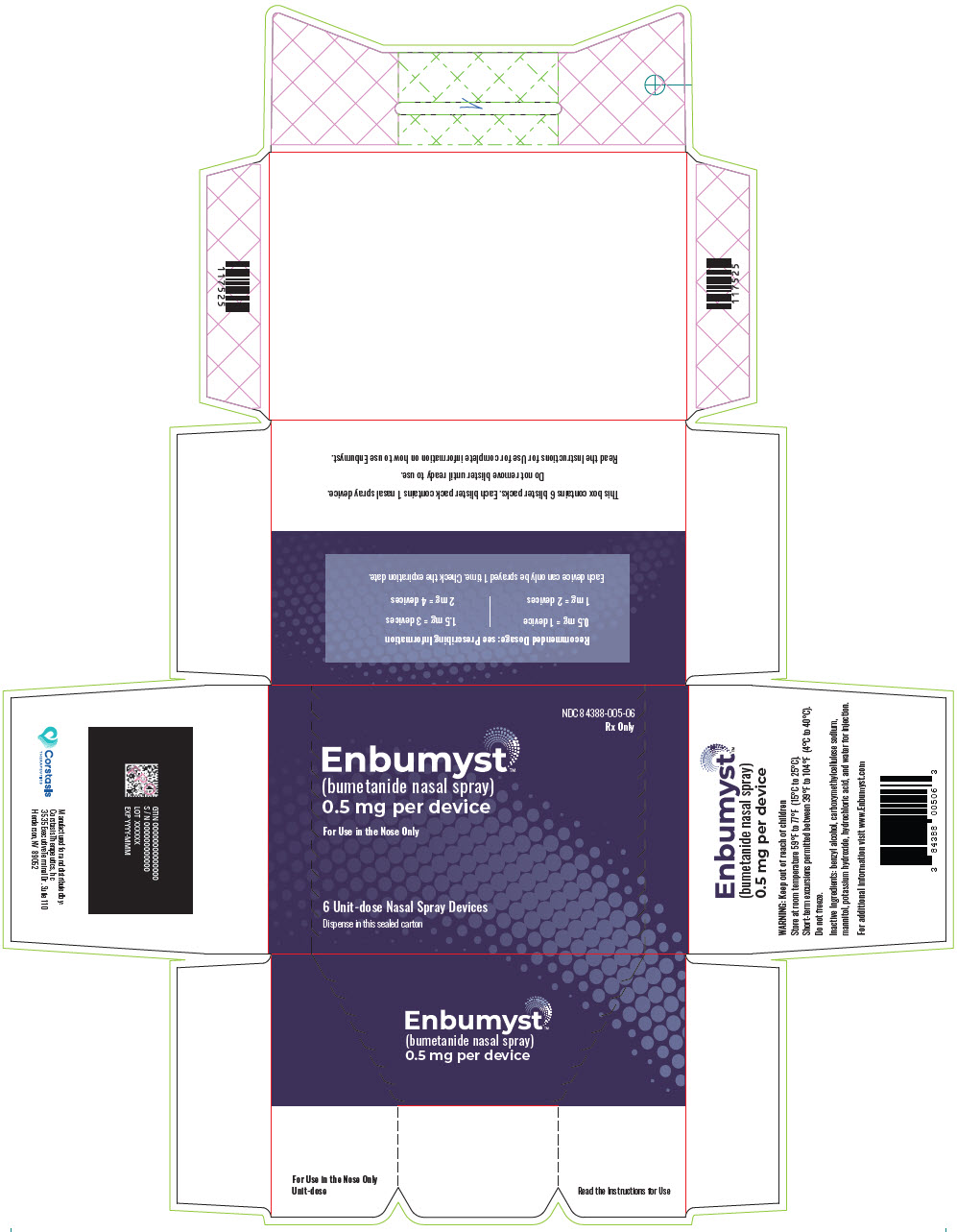 DRUG LABEL: Enbumyst
NDC: 84388-005 | Form: SPRAY
Manufacturer: Corstasis USA LLC
Category: prescription | Type: HUMAN PRESCRIPTION DRUG LABEL
Date: 20251212

ACTIVE INGREDIENTS: bumetanide 0.5 mg/0.1 mL

HIGHLIGHTS OF PRESCRIBING INFORMATION

These highlights do not include all the information needed to use ENBUMYST safely and effectively. See full prescribing information for ENBUMYST.
ENBUMYST (bumetanide nasal spray)
Initial U.S. Approval: 1983

1 INDICATIONS AND USAGE

ENBUMYST is a loop diuretic indicated for the treatment of edema associated with congestive heart failure, hepatic and renal disease, including nephrotic syndrome in adults. (1)

2 DOSAGE AND ADMINISTRATION

ENBUMYST is for nasal route only. (2)

Individualize dosage based on patient response. The recommended total daily dosage of ENBUMYST is 0.5 mg to 2 mg administered once daily. (2.1)

ENBUMYST is not intended for chronic use; replace with oral diuretics as soon as practical. (2.1)

3 DOSAGE FORMS AND STRENGTHS

Nasal spray: 0.5 mg bumetanide per 0.1 mL spray

4 CONTRAINDICATIONS

- Anuria. (4)
- Hepatic coma. (4)
- History of hypersensitivity to bumetanide. (4)

5 WARNINGS AND PRECAUTIONS

- Fluid, Electrolyte, and Metabolic Abnormalities: Monitor serum electrolytes, CO2, BUN, creatinine, glucose and uric acid. (5.1)
- Worsening Renal Function: Monitor for dehydration and azotemia. (5.2)
- Ototoxicity: Avoid higher than recommended doses. (5.3)
- Potential Altered Absorption in Patients with Nasal Mucosal or Structural Abnormalities: Avoid use in patients with significant nasal mucosal or structural abnormalities, such as acute episodes of rhinitis or congestion due to any cause. (5.4)

6 ADVERSE REACTIONS

Most common adverse reactions (incidence > 0.5%) are hypovolemia, headache, muscle cramps, dizziness, hypotension, nausea and encephalopathy (in patients with pre-existing liver disease). (6)

To report SUSPECTED ADVERSE REACTIONS, contact Corstasis Therapeutics at 1-877-300-5339 or FDA at 1-800-FDA-1088 or www.fda.gov/medwatch.

7 DRUG INTERACTIONS

- Lithium may reduce renal clearance of bumetanide and add a high risk of lithium toxicity. (7)
- Probenecid reduces both the natriuresis and hyperreninemia. (7)
- Indomethacin blunts the increase in urine volume and sodium excretion. (7)
- Drugs with ototoxic potential: avoid parenteral bumetanide in patients receiving aminoglycoside antibiotics. (7)
- Drugs with nephrotoxic potential: the simultaneous administration of ENBUMYST with drugs of nephrotoxic potential should be avoided. (7)
- Antihypertensive effects may be potentiated by bumetanide. (7)

8 USE IN SPECIFIC POPULATIONS

- Lactation: A lactating woman treated with ENBUMYST should monitor her infant for excessive urine output, dehydration, and lethargy. (8.2)

FULL PRESCRIBING INFORMATION

1 INDICATIONS AND USAGE

ENBUMYST is indicated for the treatment of edema associated with congestive heart failure, hepatic and renal disease, including the nephrotic syndrome in adults.

2 DOSAGE AND ADMINISTRATION

2.1 Recommended Dosage

Each unit-dose nasal spray contains 0.5 mg of bumetanide. The usual total daily dosage of ENBUMYST is 0.5 mg to 2 mg once daily. The number of nasal spray devices needed for a single dose depends upon the prescribed dose. Individualize dosage based on patient response up to a maximum dose of 2 mg/day.

ENBUMYST is not intended for chronic use and should be replaced with oral diuretics as soon as practical.

ENBUMYST can be substituted at approximately a 1:40 ratio to oral furosemide and a 1:20 ratio to intravenous furosemide.

2.2 Administration Instructions

- ENBUMYST is for nasal use only.
- Each ENBUMYST unit is for single use and delivers 0.5 mg bumetanide upon actuation.
- Do not prime or attempt to reuse ENBUMYST for more than one administration.
- Administer ENBUMYST directly into the nose and not against the wall of the nose.
- If prescribed dose requires more than one nasal spray, alternate between right and left nostrils.

Refer patients and caregivers to the Instructions for Use for detailed administration instructions.

3 DOSAGE FORMS AND STRENGTHS

Nasal spray: 0.5 mg bumetanide per 0.1 mL spray in a unit-dose nasal spray.

4 CONTRAINDICATIONS

Bumetanide is contraindicated in:

- Patients with anuria.
- Patients in hepatic coma.
- Patients with a history of a hypersensitivity reaction to bumetanide. Reactions have included anaphylaxis and anaphylactoid reactions.

5 WARNINGS AND PRECAUTIONS

5.1 Fluid, Electrolyte, and Metabolic Abnormalities

Bumetanide may cause fluid, electrolyte, and metabolic abnormalities such as hypovolemia, hypokalemia, azotemia, hyponatremia, hypochloremic alkalosis, hypomagnesemia, hypocalcemia, hyperglycemia, or hyperuricemia, particularly in patients receiving higher doses, patients with inadequate oral electrolyte intake, and in elderly patients. Excessive diuresis may cause dehydration and blood volume reduction with circulatory collapse and possibly vascular thrombosis and embolism, particularly in elderly patients. Serum electrolytes, CO2, BUN, creatinine, glucose, and uric acid should be monitored frequently during bumetanide therapy.

5.2 Worsening Renal Function

Bumetanide can cause dehydration and azotemia. If increasing azotemia and oliguria occur during treatment of severe progressive renal disease, discontinue bumetanide [see Clinical Pharmacology (12.3)].

5.3 Ototoxicity

Tinnitus and hearing loss (usually reversible) have been reported with loop diuretics, including bumetanide. Reports indicate that ototoxicity is associated with rapid injection, severe renal impairment, the use of higher than recommended doses, hypoproteinemia or concomitant therapy with aminoglycoside antibiotics, ethacrynic acid, or other ototoxic drugs.

5.4 Potential Altered Absorption in Patients with Nasal Mucosal or Structural Abnormalities

ENBUMYST has not been assessed in individuals with nasal mucosal or structural abnormalities. Avoid use in patients with significant nasal mucosal or structural abnormalities, such as acute episodes of rhinitis or congestion due to any cause. Consider alternative products or therapies in such patients.

6 ADVERSE REACTIONS

The following clinically significant adverse reactions are described elsewhere in the labeling:

- Fluid, electrolyte, and metabolic abnormalities [see Warnings and Precautions (5.1)]
- Worsening Renal Function [see Warnings and Precautions (5.2)]
- Ototoxicity [see Warnings and Precautions (5.3)]
- Potential Altered Absorption in Patients with Nasal Mucosal or Structural Abnormalities [see Warnings and Precautions (5.4)]

Because clinical trials are conducted under widely varying conditions, adverse reaction rates observed in the clinical trials of a drug cannot be directly compared to rates in the clinical trials of another drug and may not reflect the rates observed in practice.

The safety of ENBUMYST is supported by clinical trials and postmarketing reports of oral bumetanide, as well as open-label, single- and repeat-dose studies of ENBUMYST in healthy subjects.

Adverse Reactions in Two Clinical Pharmacology Studies with ENBUMYST in Adult Subjects

In open-label studies of ENBUMYST in healthy subjects (n = 84), the most common adverse reaction that occurred with ENBUMYST was hypovolemia (4.8%) [see Warnings and Precautions (5.1)]. Headache occurred in 3% of subjects. There were no adverse reactions specifically associated with the nasal route of administration such as nasal irritation or pain. There was a single case of nasal dryness.

Adverse Reactions in Studies with Oral Bumetanide

The following adverse reactions were identified in clinical studies or postmarketing reports with the use of oral bumetanide. Because some of these reactions were reported voluntarily from a population of uncertain size, it is not always possible to reliably estimate their frequency or establish a causal relationship to drug exposure.

The most frequent clinical adverse reactions considered probably or possibly related to oral bumetanide are muscle cramps (seen in 1.1% of treated patients), dizziness (1.1%), hypotension (0.8%), headache (0.6%), nausea (0.6%) and encephalopathy (in patients with pre-existing liver disease) (0.6%). One or more of these adverse reactions have been reported in approximately 4.1% of patients treated with bumetanide.

The following additional adverse reactions have been reported with bumetanide.

Blood and Lymphatic System Disorders: Deviations in hemoglobin, prothrombin time, hematocrit, WBC and differential counts, thrombocytopenia

Cardiac Disorders: Chest pain, electrocardiogram changes

Ear and Labyrinth Disorders: Ear discomfort, impaired hearing, vertigo

Gastrointestinal Disorders: Abdominal pain, diarrhea, dry mouth, GI upset, vomiting

General Disorders and Administration Site Conditions: Fatigue, weakness

Investigations: Changes in LDH, total serum bilirubin, serum proteins, SGOT, SGPT, alkaline phosphatase, cholesterol, creatinine clearance, urinary glucose, and urinary protein

Metabolism and Nutrition Disorders: Dehydration

Musculoskeletal and Connective Tissue Disorders: Arthritic pain, musculoskeletal pain

Nervous System Disorders: Asterixis

Renal and Urinary Disorders: Renal failure

Reproductive System and Breast Disorders: Erectile dysfunction, nipple tenderness, premature ejaculation

Respiratory, Thoracic and Mediastinal Disorders: Hyperventilation

Skin and Subcutaneous Tissue Disorders: Pruritus, rash, Stevens-Johnson syndrome, sweating, toxic epidermal necrolysis

7 DRUG INTERACTIONS

7.1 Effects of Other Drugs on Bumetanide

Lithium

Lithium should generally not be given with diuretics (such as bumetanide) because they reduce its renal clearance and add a high risk of lithium toxicity.

Probenecid

Probenecid should not be administered concurrently with bumetanide. Pretreatment with probenecid reduces both the natriuresis and hyperreninemia produced by bumetanide. This antagonistic effect of probenecid on bumetanide natriuresis is not due to a direct action on sodium excretion but is probably secondary to its inhibitory effect on renal tubular secretion of bumetanide.

Indomethacin

Concurrent therapy with bumetanide is not recommended. Indomethacin blunts the increases in urine volume and sodium excretion seen during bumetanide treatment and inhibits the bumetanide-induced increase in plasma renin activity.

7.2 Effects of Bumetanide on Other Drugs

Drugs with Ototoxic Potential [see Warnings and Precautions (5.3)]

Especially in the presence of impaired renal function, the use of parenterally administered bumetanide in patients to whom aminoglycoside antibiotics are also being given should be avoided, except in life-threatening conditions.

Drugs with Nephrotoxic Potential

Monitor renal function. Concomitant use may worsen renal function and increase the risk of nephrotoxicity.

Antihypertensives

Bumetanide may potentiate the effect of various antihypertensive drugs, necessitating a reduction in the dosage of these drugs.

Digoxin

Interaction studies in humans have shown no effect on digoxin blood levels.

Anticoagulants

Interaction studies in humans have shown bumetanide to have no effect on warfarin metabolism or on plasma prothrombin activity.

8 USE IN SPECIFIC POPULATIONS

8.1 Pregnancy

Risk Summary

The available data on bumetanide use in pregnant women from scientific review publications have not identified a drug-associated risk of major birth defects, miscarriage, or other adverse maternal or fetal outcomes. Untreated congestive heart failure, hepatic disease such as cirrhosis and chronic kidney disease can lead to adverse outcomes for the mother and fetus (see Clinical Considerations).

In animal reproduction studies, no malformations were observed with oral administration of bumetanide to pregnant rats and rabbits during organogenesis at doses approximately 485 times and equivalent to a human dose of 2 mg once daily, respectively (see Data).

The background risk for major birth defects and miscarriage for the indicated populations is unknown. All pregnancies have a background risk of birth defect, loss, or other adverse outcomes. In the U.S. general population, the background risk of major birth defects and miscarriage in the clinically recognized pregnancies is 2 to 4% and 15 to 20%, respectively.

Clinical Considerations

Disease-Associated Maternal and/or Embryo/Fetal Risk

Pregnant women with congestive heart failure are at increased risk for pre-term birth. Stroke volume and heart rate increase during pregnancy, increasing cardiac output, especially during the first trimester. Clinical classification of heart disease may worsen with pregnancy and lead to maternal death and/or stillbirth. Closely monitor pregnant patients for destabilization of their heart failure.

Pregnant women with symptomatic cirrhosis generally have poor outcomes including hepatic failure, variceal hemorrhage, pre-term delivery, fetal growth restriction and maternal death. Outcomes are worse with coexisting esophageal varices. Pregnant women with cirrhosis of the liver should be carefully monitored and managed accordingly.

Chronic kidney disease in pregnancy increases the risk for maternal hypertension and preeclampsia, miscarriage, preterm delivery, polyhydramnios, still birth, and low birth weight infants.

Data

Animal Data

Bumetanide has been shown to be nonteratogenic, but it has a slight embryocidal effect in rats when given at a dose approximately 485 times and in rabbits at a dose equivalent to a 2 mg/day human dose, based on body surface area (BSA). In one study, moderate growth retardation and increased incidence of delayed ossification of sternebrae were observed in rats at oral doses of 100 mg/kg/day, approximately 485 times a 2 mg/day human dose, based on BSA. These effects were associated with maternal weight reductions noted during dosing. No such adverse effects were observed at 30 mg/kg/day (approximately 146 times a 2 mg/day human dose, based on BSA). No fetotoxicity was observed at dose up to approximately 292 times a 2 mg/day human dose, based on BSA.

In rabbits, a dose-related decrease in litter size and an increase in resorption rate were noted at oral doses of 0.1 mg/kg/day and 0.3 mg/kg/day (approximately equivalent to 3 times a 2 mg/day human dose, based on BSA). A slightly increased incidence of delayed ossification of sternebrae occurred at 0.3 mg/kg/day; however, no such adverse effects were observed at the dose of 0.03 mg/kg/day. The sensitivity of the rabbit to bumetanide parallels the marked pharmacologic and toxicologic effects of the drug in this species.

Bumetanide was not teratogenic in the hamster at an oral dose of 0.5 mg/kg/day (approximately 3 times a 2 mg/day human dose, based on BSA).

8.2 Lactation

Risk Summary

There are no data on the presence of bumetanide in either human or animal milk, the effects on the breastfed infant, or the effects on milk production. Because there have been no reports of adverse events in breastfed infants over decades of bumetanide use, the developmental and health benefits of breastfeeding should be considered along with the mother's clinical need for bumetanide and any potential adverse effects on the breastfed infant from bumetanide or from the underlying maternal condition.

Clinical Considerations

Monitor infants potentially exposed to ENBUMYST through breast milk for excessive urine output, dehydration and lethargy.

8.4 Pediatric Use

The safety and effectiveness of ENBUMYST (bumetanide nasal spray) have not been established in pediatric patients.

In vitro studies using pooled sera from critically ill neonates have shown bumetanide to be a potent displacer of bilirubin. The administration of bumetanide could present a particular concern if given to critically ill or jaundiced neonates at risk for kernicterus. ENBUMYST (bumetanide nasal spray) is not approved for use in pediatric patients, including neonates.

8.5 Geriatric Use

Clinical studies of bumetanide did not include sufficient numbers of subjects aged 65 and over to determine whether they responded differently from younger subjects. Other reported clinical experience has not identified differences in responses between the elderly and younger patients. In general, dose selection for an elderly patient should be cautious, usually starting at the low end of the dosing range, reflecting the greater frequency of decreased hepatic, renal or cardiac function and of concomitant disease or other drug therapy.

This drug is known to be substantially excreted by the kidney, and the risk of toxic reactions to this drug may be greater in patients with impaired renal function. Because elderly patients are more likely to have decreased renal function, care should be taken in dose selection, and it may be useful to monitor renal function.

10 OVERDOSAGE

Overdosage can lead to acute profound water loss, volume and electrolyte depletion, dehydration, reduction of blood volume and circulatory collapse with a possibility of vascular thrombosis and embolism. Electrolyte depletion may be manifested by weakness, dizziness, mental confusion, anorexia, lethargy, vomiting and cramps. Treatment consists of replacement of fluid and electrolyte losses by careful monitoring of the urine and electrolyte output and serum electrolyte levels.

11 DESCRIPTION

ENBUMYST contains bumetanide, a loop diuretic. Chemically, bumetanide is 3-(butylamino)-4-phenoxy-5-sulfamoylbenzoic acid. It is a practically white powder with a calculated molecular weight of 364.42 g/mol, and the following structural formula:

ENBUMYST is supplied as a unit-dose nasal spray containing 0.5 mg of bumetanide (equivalent to about 0.554 mg of potassium salt of bumetanide) per 0.1 mL. ENBUMYST contains the following inactive ingredients: benzyl alcohol (0.5 mg per 0.1 mL spray), carboxymethylcellulose sodium (viscosity control agent), mannitol, potassium hydroxide (pH modifier), hydrochloric acid (to adjust pH) and water for injection.

12 CLINICAL PHARMACOLOGY

12.1 Mechanism of Action

Bumetanide primarily inhibits the reabsorption of sodium and chloride in the proximal and distal tubules and in the loop of Henle. The high degree of diuresis is largely due to the unique site of action. The action on the distal tubule is independent of any inhibitory effect on carbonic anhydrase and aldosterone.

12.2 Pharmacodynamics

Following administration of ENBUMYST, the onset of diuresis occurs in less than 60 minutes. Peak activity is reached between 0.75 and 1.5 hours. At a maximum dose of 2 mg, diuresis is largely complete within 4 hours. Bumetanide decreases uric acid excretion and increases serum uric acid.

In a study in 68 healthy adults, the effect of 2 mg ENBUMYST on diuresis, natriuresis and potassium urine excretion over 0 to 8 hours and 0 to 24 hours was similar to that of 2 mg bumetanide oral tablet and 2 mg bumetanide IV injection.

12.3 Pharmacokinetics

In a study in healthy adults, the exposure (Cmax and AUC) of 2 mg ENBUMYST was similar to that of 2 mg bumetanide oral tablet. The exposure of 2 mg ENBUMYST was approximately 11% (Cmax) and 65-67% (AUC) relative to that of 2 mg bumetanide IV injection.

Absorption

Bumetanide median time to maximum concentration (Tmax) is 1.0 hour following nasal administration of ENBUMYST.

Distribution

Bumetanide exhibits high plasma protein binding in the range of 94% to 96%.

Elimination

Bumetanide is eliminated rapidly in humans following both oral and parenteral (intravenous or intramuscular) administration, with a half-life of 1 to 1.5 hours. ENBUMYST demonstrated a half-life of approximately 3 hours in healthy adult subjects.

Metabolism

Mass balance studies using carbon-14 labeled bumetanide in healthy adults identified metabolites formed by oxidation of the N-butyl side chain. These metabolites were detected in both urine and bile.

Excretion

Following oral administration of carbon-14 labeled bumetanide to healthy adults, 81% of the administered radioactivity was recovered in urine, with 45% excreted as unchanged drug. Biliary excretion accounted for 2% of the administered dose.

Specific Populations

Geriatric Patients

In a group of ten geriatric subjects between the ages of 65 and 73 years, total bumetanide clearance was significantly lower (1.8 ± 0.3 mL/min*kg) compared with younger subjects (2.9 ± 0.2 mL/min*kg) after a single oral bumetanide 0.5 mg dose. Maximum plasma concentrations were higher in geriatric subjects (16.9 ± 1.8 ng/mL) compared with younger subjects (10.3 ± 1.5 ng/mL). Urine flow rate and total excretion of sodium and potassium were increased less in the geriatric subjects compared with younger subjects, although potassium excretion and fractional sodium excretion were similar between the two age groups. Nonrenal clearance, bioavailability, and volume of distribution were not significantly different between the two groups.

13 NONCLINICAL TOXICOLOGY

13.1 Carcinogenesis, Mutagenesis, Impairment of Fertility

Bumetanide was devoid of mutagenic activity in various strains of Salmonella typhimurium when tested in the presence or absence of an in vitro metabolic activation system. An 18-month study showed an increase in mammary adenomas of questionable significance in female rats receiving oral doses of 60 mg/kg/day (approximately 290 times a 2 mg/day human dose, based on BSA). A repeat study at the same doses failed to duplicate this finding.

Reproduction studies were performed to evaluate general reproductive performance and fertility in rats at oral dose levels of 10 mg/kg/day, 30 mg/kg/day, 60 mg/kg/day or 100 mg/kg/day. The pregnancy rate was slightly decreased in the treated animals; however, the differences were small and not statistically significant.

16 HOW SUPPLIED/STORAGE AND HANDLING

How Supplied

ENBUMYST is a clear, colorless solution, supplied as a 12-pack carton containing unit-dose nasal sprays as shown in Table 1. Each unit-dose nasal spray delivers 0.5 mg bumetanide.

Table 1: Available Packaging Configurations
Description | Package Configuration | NDC
12-pack carton | Two (2) 6-pack cartons containing twelve (12) blister packages each with a unit-dose nasal spray | NDC 84388-005-12

Storage and Handling

Store at room temperature 59°F to 77°F (15°C to 25°C). Short-term excursions permitted between 39°F to 104°F (4°C to 40°C). Do not freeze. Dispense in the original sealed carton.

17 PATIENT COUNSELING INFORMATION

Advise the patient to read the FDA-approved patient labeling (Patient Information and Instructions for Use).

Administration

Advise patients on appropriate administration, including the number of devices to use [see Dosage and Administration (2)].

Lactation

Advise lactating women treated with ENBUMYST to monitor their breastfed infant for excessive urine output, dehydration, and lethargy [see Use in Specific Populations (8.2)].

Manufactured for Corstasis Therapeutics, 3535 Executive Terminal Drive, Henderson, NV 89042
Copyright © 2025 Corstasis Therapeutics. All rights reserved

PATIENT INFORMATION
ENBUMYST (En-byoo-mist)
(bumetanide nasal spray)

What is the most important information I should know about ENBUMYST?

- ENBUMYST is a diuretic that causes fluid loss and may lead to abnormalities with blood electrolytes and body energy systems (metabolic). Too much fluid loss can lead to dehydration and decreased blood volume and increase your risk of blood clots. Blood abnormalities may include decreased salts (electrolytes), and increased nitrogen, glucose and uric acid. The chance of getting these abnormalities is higher in people who are elderly, use higher doses, or who do not get enough electrolytes by mouth. Your healthcare provider should do blood tests to check for these abnormalities during treatment with ENBUMYST.
- You should not use ENBUMYST if you have severe electrolyte loss until it gets better.

Tell your healthcare provider if you get any of the following signs or symptoms:

- unusual thirst
- dizziness or lightheadedness
- weakness or tiredness
- fast heart rate
- dry mouth or tongue
- sudden pain, redness or swelling in your joints, especially your big toe (gout)
- pain, swelling, redness, or warmth in your leg

- shortness of breath
- fast breathing
- high blood sugar
- dark urine
- skin is pale, tight, cool or clammy
- muscle cramps
- confusion

- See "What are the possible side effects of ENBUMYST?" for more information about side effects.

What is ENBUMYST?
ENBUMYST is a prescription medicine used in adults to treat swelling caused by too much fluid in the body (edema) from congestive heart failure, liver disease and kidney disease, including a kidney problem called nephrotic syndrome.
It is not known if ENBUMYST is safe and effective in children.

Who should not use ENBUMYST?

Do not use ENBUMYST if you:

- have very low or no urine production
- are allergic to bumetanide or to any of the ingredients in ENBUMYST. See the end of this Patient Information for a complete list of ingredients in ENBUMYST.

Before using ENBUMYST, tell your healthcare provider about all your medical conditions, including if you:

- have low levels of salts (electrolytes) in your blood, or are on a low-salt diet
- have diarrhea
- have diabetes
- have nasal problems including a runny nose, nasal congestion, nasal polyps, history of injury such as a broken nose, or any past nasal surgery
- are pregnant or plan to become pregnant. It is not known if ENBUMYST will harm your unborn baby.
- are breastfeeding or plan to breastfeed. It is not known if ENBUMYST passes into your breast milk. If you use ENBUMYST and breastfeed, watch your baby for signs of urinating more than usual, dehydration, or unusual sleepiness, drowsiness, or sluggishness.

Tell your healthcare provider about all the medicines you take, including prescription and over-the-counter medicines, vitamins and herbal supplements.
ENBUMYST and other medicines may affect each other, causing side effects, and may affect the way each other works.

Especially tell your healthcare provider if you take or use:

- other nasal sprays
- water pills (diuretics)
- lithium
- probenecid

- indomethacin
- antibiotic medicines called aminoglycosides
- medicines to treat high blood pressure

Know the medicines you take. Keep a list of them to show your healthcare provider and pharmacist when you get a new medicine.

How should I use ENBUMYST?

- Read the Instructions for Use that come with ENBUMYST for detailed information about how to use the device.
- Use ENBUMYST exactly as your healthcare provider tells you to. Talk to your healthcare provider or pharmacist if you have questions about how to use ENBUMYST.
- ENBUMYST is for use in the nose only.
- Each ENBUMYST device has 1 spray of medicine and cannot be reused. Do not test or prime (pre-spray) the device.
- ENBUMYST comes in a carton with 12 devices. Use the following number of nasal spray devices for your prescribed dose:

Prescribed Dose

Number of Nasal Spray Devices

0.5 mg

1 device

1 mg

2 devices

1.5 mg

3 devices

2 mg

4 devices

- Your healthcare provider will prescribe the dose of ENBUMYST that is right for you.
- ENBUMYST is for short term use only for a single treatment course (episode) of edema.
- If you use too much ENBUMYST call your healthcare provider right away.

What are the possible side effects of ENBUMYST?

ENBUMYST may cause serious side effects, including:

- See "What is the most important information I should know about ENBUMYST?"
- Worsening kidney function. Your healthcare provider may stop treatment if your kidney function gets worse.
- Ear damage (ototoxicity) including ringing in the ears (tinnitus) or hearing loss, especially in people with severe kidney problems, taking higher than recommended doses, with low levels of protein in the blood, and when used with certain other medicines.

The most common side effects of ENBUMYST include:

- low levels of fluid in the body
- headache
- muscle cramps
- dizziness

- low blood pressure
- nausea
- abnormal brain functioning in people with certain liver problems

Tell your healthcare provider if you have any side effect that bothers you or that does not go away.
These are not all the possible side effects of ENBUMYST.
Call your doctor for medical advice about side effects. You may report side effects to FDA at 1-800-FDA-1088.

How should I store ENBUMYST?

- Store ENBUMYST at room temperature between 59°F to 77°F (15°C to 25°C).
- Do not freeze.

Keep ENBUMYST and all medicines out of the reach of children.

General information about the safe and effective use of ENBUMYST.
Medicines are sometimes prescribed for purposes other than those listed in a Patient Information leaflet. Do not use ENBUMYST for a condition for which it was not prescribed. Do not give ENBUMYST to other people, even if they have the same symptoms that you have. It may harm them. You can ask your pharmacist or healthcare provider for information about ENBUMYST that is written for health professionals.

What are the ingredients in ENBUMYST?
Active Ingredient: bumetanide
Inactive Ingredients: benzyl alcohol (0.5 mg per 0.1 mL spray), carboxymethylcellulose sodium, mannitol, potassium hydroxide (pH modifier), hydrochloric acid (to adjust pH) and water for injection.
Manufactured for Corstasis Therapeutics, 3535 Executive Terminal Drive, Henderson, NV 89042
Copyright © 2025 Corstasis Therapeutics. All rights reserved.
For more information about ENBUMYST, call 1-877-300-5339 or visit ENBUMYST.com.

This Patient Information has been approved by the U.S. Food and Drug Administration.

Revised: November 2025

PRINCIPAL DISPLAY PANEL - 0.5 mg Device Blister Pack Carton

NDC 84388-005-06
Rx Only

Enbumyst™
(bumetanide nasal spray)
0.5 mg per device

For Use in the Nose Only

6 Unit-dose Nasal Spray Devices

Dispense in this sealed carton